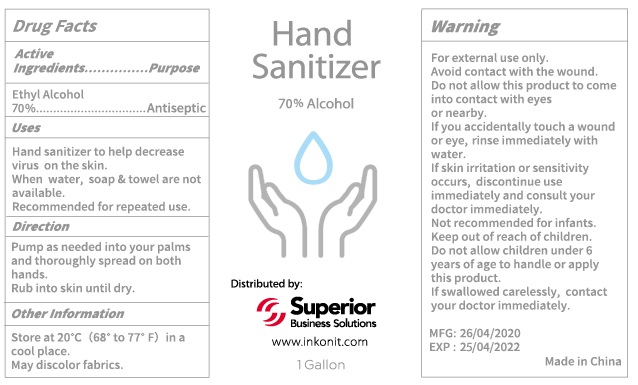 DRUG LABEL: Hand Sanitizer
NDC: 71734-302 | Form: GEL
Manufacturer: JIANGMEN SHUIZIRUN SANITARY ARTICLES CO., LTD.
Category: otc | Type: HUMAN OTC DRUG LABEL
Date: 20200417

ACTIVE INGREDIENTS: ALCOHOL 70 mL/100 mL
INACTIVE INGREDIENTS: WATER; GLYCERIN; TROLAMINe; EDETATE DISODIUM

Active ingredient

70% Ethyl Alcohol

Purpose

Antiseptic

Use

Hand sanitizer to help decrease virus on the skin.

When water, soap and towel are not available

Recommended for repeated use.

Warnings

For external use only.

For external use only.

Avoid contact with the wound.

Do not allow this product to come or nearby.

If you accidentally touch a wound or eye, rinse immediately with water.

If skin irritation or sensitivity occurs, discontinue use immediately and consult your doctor imediately.

Not recommended for infants.

Keep out of reach of children.

Do not allow children under 6 years of age to handle or apply this product.

If swallowed carelessly, contact your doctor immediately.

Directions

Pump as needed into your palms and thoroughly spread on both hands.

Rub into skin until dry.

Inactive ingredients

Pure Water, Glycerin, Carbomer, Triethanolamine, Disodium EDTA

Other Information

Store at 20 ℃ （68 to 77 ℉）in a cool place.

May discolor fabrics.